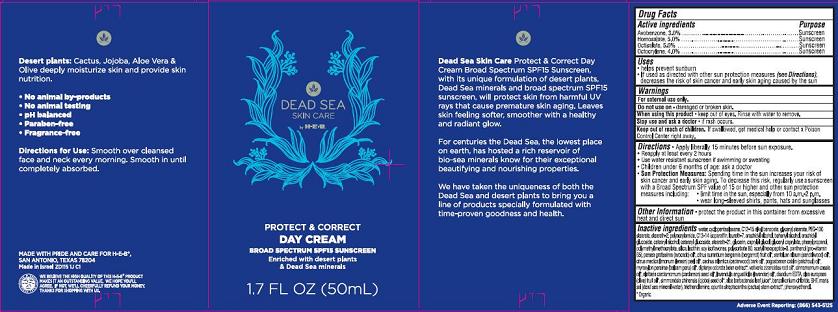 DRUG LABEL: H-E-B Dead Sea Organics Protect and Perfect Day Broad Spectrum SPF15
NDC: 42421-115 | Form: CREAM
Manufacturer: Emilia Personal Care Inc.
Category: otc | Type: HUMAN OTC DRUG LABEL
Date: 20140113

ACTIVE INGREDIENTS: AVOBENZONE 3 g/100 mL; HOMOSALATE 5 g/100 mL; OCTISALATE 5 g/100 mL; OCTOCRYLENE 4 g/100 mL
INACTIVE INGREDIENTS: WATER; CYCLOMETHICONE 5; ALKYL (C12-15) BENZOATE; GLYCERYL MONOSTEARATE; PEG-100 STEARATE; STEARETH-2; POLYACRYLAMIDE (10000 MW); C13-14 ISOPARAFFIN; LAURETH-7; ARACHIDYL ALCOHOL; DOCOSANOL; ARACHIDYL GLUCOSIDE; CETOSTEARYL ALCOHOL; CETEARYL GLUCOSIDE; STEARETH-21; GLYCERIN; CAPRYLYL GLYCOL; GLYCERYL CAPRYLATE; PHENYLPROPANOL; POLY(METHYL METHACRYLATE; 450000 MW); SILICON DIOXIDE; LECITHIN, SOYBEAN; SOY ISOFLAVONES; POLYSORBATE 80; ACETYL HEXAPEPTIDE-8; PANTHENOL; AVOCADO OIL; BERGAMOT OIL; SANDALWOOD OIL; LEMON OIL; CEDRUS ATLANTICA BARK OIL; PATCHOULI OIL; BALSAM PERU OIL; DIPTERYX ODORATA SEED; VETIVER OIL; CHINESE CINNAMON OIL; CARDAMOM OIL; LAVENDER OIL; EDETATE DISODIUM; OLIVE OIL; JOJOBA OIL; ALOE VERA LEAF; BENZALKONIUM CHLORIDE; BUTYLATED HYDROXYTOLUENE; TROLAMINE; OPUNTIA STREPTACANTHA STEM; PHENOXYETHANOL

DEAD SEA SKIN CARE by H-E-B.
PROTECT & CORRECT DAY CREAM
BROAD SPECTRUM SPF15 SUNSCREEN

Active ingredient

Avobenzone, 3.0%
Homosalate, 5.0%
Octisalate, 5.0%
Octocrylene, 4.0%

Purpose

Sunscreen

Uses

- helps prevent sunburn
- If used as directed with other sun protection measures (see Directions), decreases the risk of skin cancer and early skin aging caused by the sun.

Warnings

For external use only.

Do not use on

- damaged or broken skin.

When using this product

- keep out of eyes. Rinse with water to remove.

Stop use and ask a doctor

if rash occurs.

Keep Out of Reach of Children

If product is swallowed, get medical help or contact a Poison Control Center right away.

Directions

- Apply liberally 15 minutes before sun exposure.
- Reapply at least every 2 hours
- Use water resistant sunscreen if swimming or sweating
- Children under 6 months: ask a doctor
- Sun Protection Measures: Spending time in the sun increases your risk of skin cancer and early skin aging. To decrease this risk, regularly use a sunscreen with a Broad Spectrum SPF value of 15 or higher and other sun protection measures including:
  - limit time in the sun, especially from 10 a.m. – 2 p.m.
  - wear long-sleeved shirts, pants, hats and sunglasses

Other Information

- protect the product in this container from excessive heat and direct sun

Inactive Ingredients

water, cyclopentasiloxane, C12-15 alkyl benzoate, glyceryl stearate, PEG-100 stearate, steareth-2, polyacrylamide, C13-14 isoparaffin, laureth-7, arachidyl alcohol, behenyl alcohol, arachidyl glucoside, cetearyl alcohol, cetearyl glucoside, steareth-21, glycerin, caprylyl glycol, glyceryl caprylate, phenylpropanol, polymethyl methacrylate, silica, lecithin, soy isoflavones, polysorbate 80, acetyl hexapeptide-8, panthenol, persea gratissima (avocado) oil*, citrus aurantium bergamia (bergamot) fruit oil*, santalum album (sandalwood) oil*, citrus medica limonum (lemon) peel oil*, cedrus atlantica (cedarwood) bark oil*, pogostomon cablin (patchouli) oil*, myroxylon pereirae (balsam peru) oil*, dipteryx odorata bean extract*, vetiveria zizanoides root oil*, cinnamomum cassia oil*, elettaria cardamomum (cardamon) seed oil*, lavandula angustifolia (lavender) oil*, disodium EDTA, olea europaea (olive) fruit oil*, simmondsia chinensis (jojoba) seed oil*, aloe barbadensis leaf juice*, benzalkonium chloride, BHT, maris sal (dead sea mineral water), triethanolamine, opuntia streptacantha (cactus) stem extract*, phenoxyethanol.

*Organic

Adverse Event Reporting:

(866) 543-5125

Package/Label Principal Display Panel

DEAD SEA SKIN CARE by H-E-B.
PROTECT & CORRECT DAY CREAM
BROAD SPECTRUM SPF15 SUNSCREEN
Enriched with desert plants & Dead Sea minerals

1.7 FL OZ (50mL)

Dead Sea Skin Care Protect & Correct Day Cream Broad Spectrum SPF15 Sunscreen, with its unique formulation of desert plants, Dead Sea minerals and broad spectrum SPF15 sunscreen, will protect skin from harmful UV rays that cause premature skin aging. Leaves skin feeling softer, smoother with a healthy and radiant glow.

For centuries the Dead Sea, the lowest place on earth, has hosted a rich reservoir of bio-sea minerals known for their exceptional beautifying and nourishing properties.

We have taken the uniqueness of both the Dead Sea and desert plants to bring you a line of products specially formulated with time-proven goodness and health.

Desert plants: Cactus, Jojoba, Aloe Vera & Olive deeply moisturize skin and provide skin nutrition.

- No animal by-products
- No animal testing
- pH balanced
- Paraben-free
- Fragrance-free

Directions for Use: Smooth over cleansed face and neck every morning. Smooth in until completely absorbed.

MADE WITH PRIDE AND CARE FOR H-E-B®,
SAN ANTONIO, TEXAS 78204
Made in Israel ZD115 1J C1

WE BELIEVE THE HIGH QUALITY OF THIS H-E-B® PRODUCT MAKES IT AN OUTSTANDING VALUE. WE HOPE YOU’LL AGREE. IF NOT, WE’LL CHEERFULLY REFUND YOUR MONEY.
THANKS FOR SHOPPING WITH US.

Carton Label